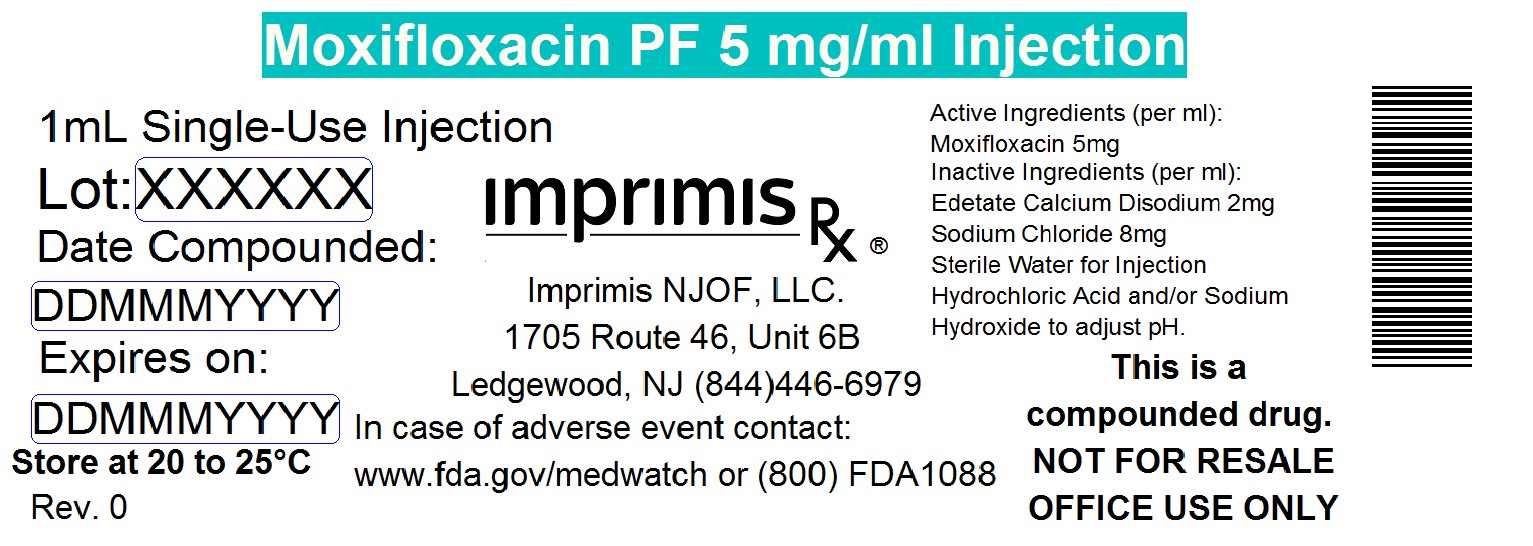 DRUG LABEL: Moxifloxacin PF
NDC: 71384-509 | Form: INJECTION, SOLUTION
Manufacturer: Imprimis NJOF, LLC
Category: prescription | Type: HUMAN PRESCRIPTION DRUG LABEL
Date: 20200303

ACTIVE INGREDIENTS: MOXIFLOXACIN HYDROCHLORIDE MONOHYDRATE 5 mg/1 mL

STORAGE AND HANDLING

Store at 20° to 25° C (68° to 77° F)